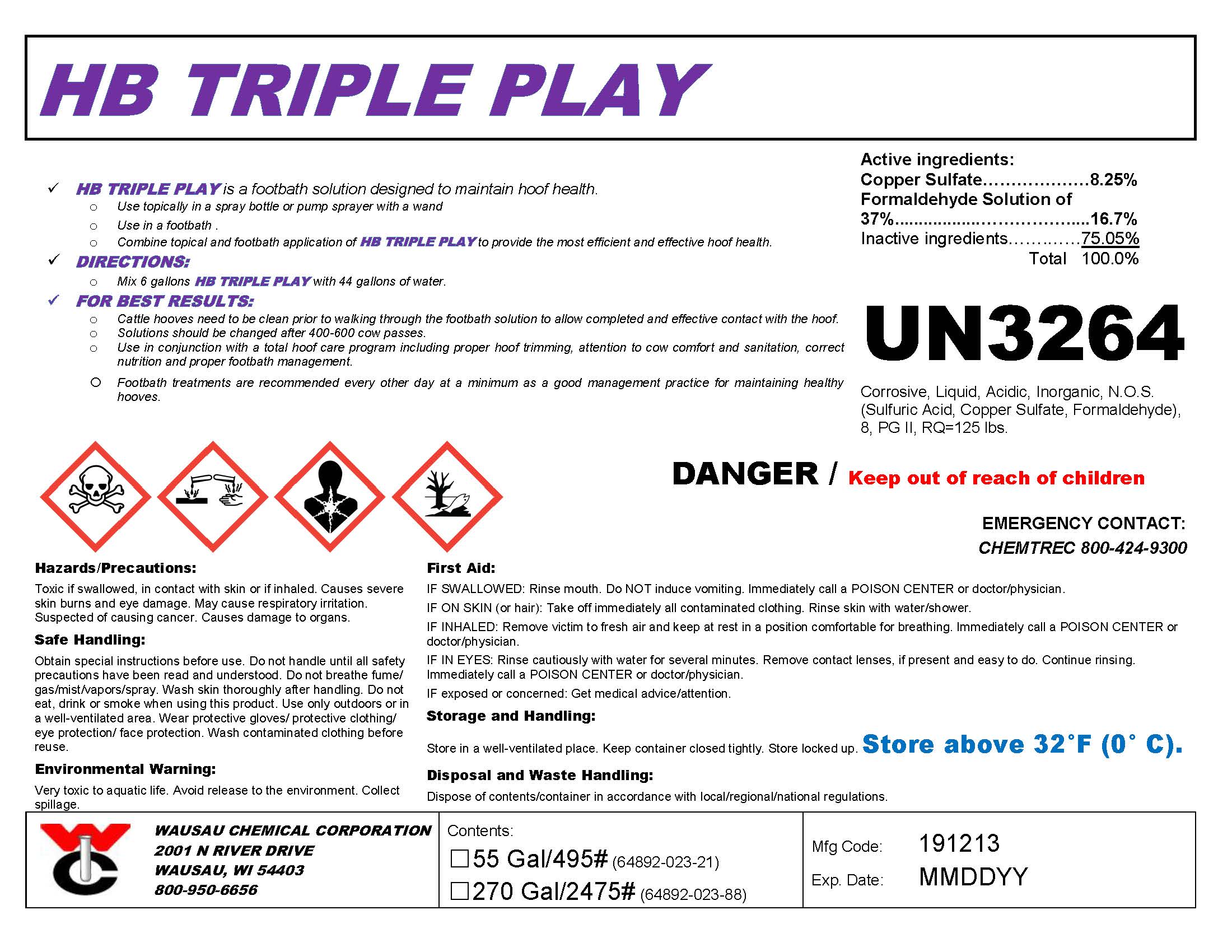 DRUG LABEL: HB Triple Play
NDC: 64892-023 | Form: SOLUTION
Manufacturer: Wausau Chemical
Category: animal | Type: OTC ANIMAL DRUG LABEL
Date: 20191213

ACTIVE INGREDIENTS: CUPRIC SULFATE, BASIC COPPER SULFATE DIBASIC 89.1 g/1 L; FORMALDEHYDE SOLUTION 399.16 1/1 L

HB Triple Play
Liquid Copper/Formaldehyde Hoof Bath Solution

DISPOSAL AND WASTE HANDLING

Dispose of contents/container in accordance with local/regional/national regulations.

ENVIRONMENTAL WARNING

Very toxic to aquatic life with long lasting effects. Avoid release to the environment. Collect spillage.

GENERAL PRECAUTIONS

DANGER / Keep Out of Reach of Children

EMERGENCY CONTACT:
CHEMTREC 800-424-9300

First Aid:

IF SWALLOWED: Rinse mouth. Do NOT induce vomiting. Immediately call a POISON CENTER or doctor/physician.
IF ON SKIN (or hair): Take off immediately all contaminated clothing. Rinse skin with water/shower.
IF INHALED: Remove victim to fresh air and keep at rest in a position comfortable for breathing. Immediately call a POISON CENTER or doctor/physician.
IF IN EYES: Rinse cautiously with water for several minutes. Remove contact lenses, if present and easy to do. Continue rinsing. Immediately call a POISON CENTER or doctor/physician.
IF exposed or concerned: Get medical advice/attention.

SAFE HANDLING WARNING

Obtain special instructions before use. Do not handle until all safety precautions have been read and understood.

Do not breathe fume/ gas/mist/vapors/spray. Wash skin thoroughly after handling. Do not eat, drink or smoke when using this product. Use only outdoors or in a well-ventilated area. Wear protective gloves/ protective clothing/ eye protection/ face protection.

Wash contaminated clothing before reuse.

STORAGE AND HANDLING

Store in a well-ventilated place. Keep container closed tightly. Store locked up.

Store above 32 °F (0 °C). If frozen, thaw and mix back into solution. Product quality will not be affected.

DIRECTIONS:
Mix 6 gallons of HB Triple Play with 44 gallons of clean water to create final solution for use in footbaths for cattle.

For best results:
Cattle hooves need to be clean prior to walking through the footbath solution to allow complete and effective contact with the hoof.
Solution should be changed after 400-600 cow passes.
Use in conjunction with a total hoof care program including proper hoof trimming, attention to cow comfort and sanitation, correct nutrition and proper footbath management.
Footbath treatments are recommended every other day at a minimum as a good management practice for maintaining healthy hooves.

Active Ingredients:

Copper Sulfate...............................................8.25%
Formaldehyde Solution of 37%......................16.7%
Inactive ingredients.....................................75.05%

Wausau Chemical Corporation

2001 N. River Drive

Wausau, WI 54403

800-950-6656